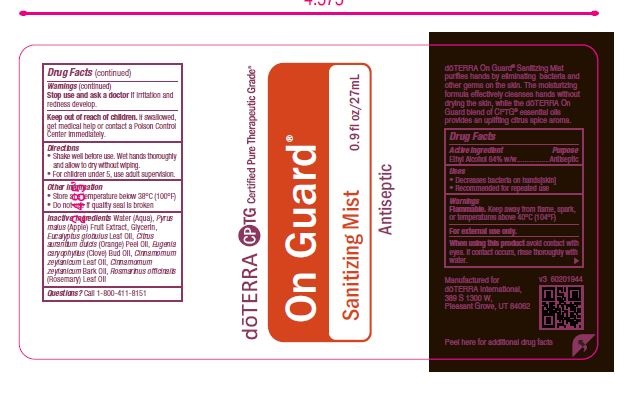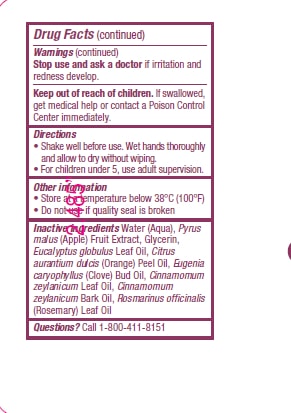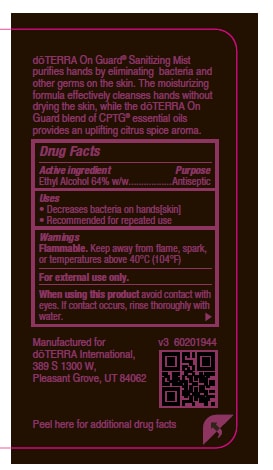 DRUG LABEL: On Guard Sanitizing Mist
NDC: 71630-718 | Form: SPRAY
Manufacturer: doTERRA International, LLC
Category: otc | Type: HUMAN OTC DRUG LABEL
Date: 20200203

ACTIVE INGREDIENTS: ALCOHOL 70 mL/100 mL
INACTIVE INGREDIENTS: WATER; ORANGE OIL; APPLE; GLYCERIN; EUCALYPTUS GLOBULUS LEAF; CINNAMON LEAF OIL; CINNAMON BARK OIL; ROSEMARY OIL; CLOVE OIL

OG Sanitizing Mist

ACTIVE INGREDIENT

Ethyl Alcohol 64% (w/w)

PURPOSE

Antiseptic

Uses
• Decreases bacteria on hands[skin]
• Recommended for repeated use

WARNINGS

Flammable. Keep away from flame, spark,
or temperatures above 40°C (104°F)

For external use only.

When using this product avoid contact with
eyes. If contact occurs, rinse thoroughly with
water.

Stop use and ask a doctor if irritation and
redness develop

Keep out of reach of children. If swallowed, get medical help or contact a Poison Control Center immediately.

Other information
• Store at a temperature below 38°C (100°F)
• Do not use if quality seal is broken

Inactive ingredients: Water (Aqua), Pyrus
malus (Apple) Fruit Extract, Glycerin,
Eucalyptus Globulus Leaf Oil, Citrus
aurantium dulcis (Orange) Peel Oil, Eugenia
caryophyllus (Clove) Bud Oil, Cinnamomum
zeylanicum Leaf Oil, Cinnamomum
zeylanicum Bark Oil, Rosmarinus officinalis
(Rosemary) Leaf Oil

Questions? Call 1-800-411-8151

Active ingredient Purpose
Alcohol 64% w/w.........................Antiseptic

Directions
• Wet hands thoroughly and allow to dry
without wiping.
• For children under 5, use adult supervision.

Principal Display Panel and Package Label

doTERRA On Guard®

Sanitizing Mist

Antiseptic

0.9 fl. oz/27 mL

CPTG Certified Pure Therapeutic Grade®